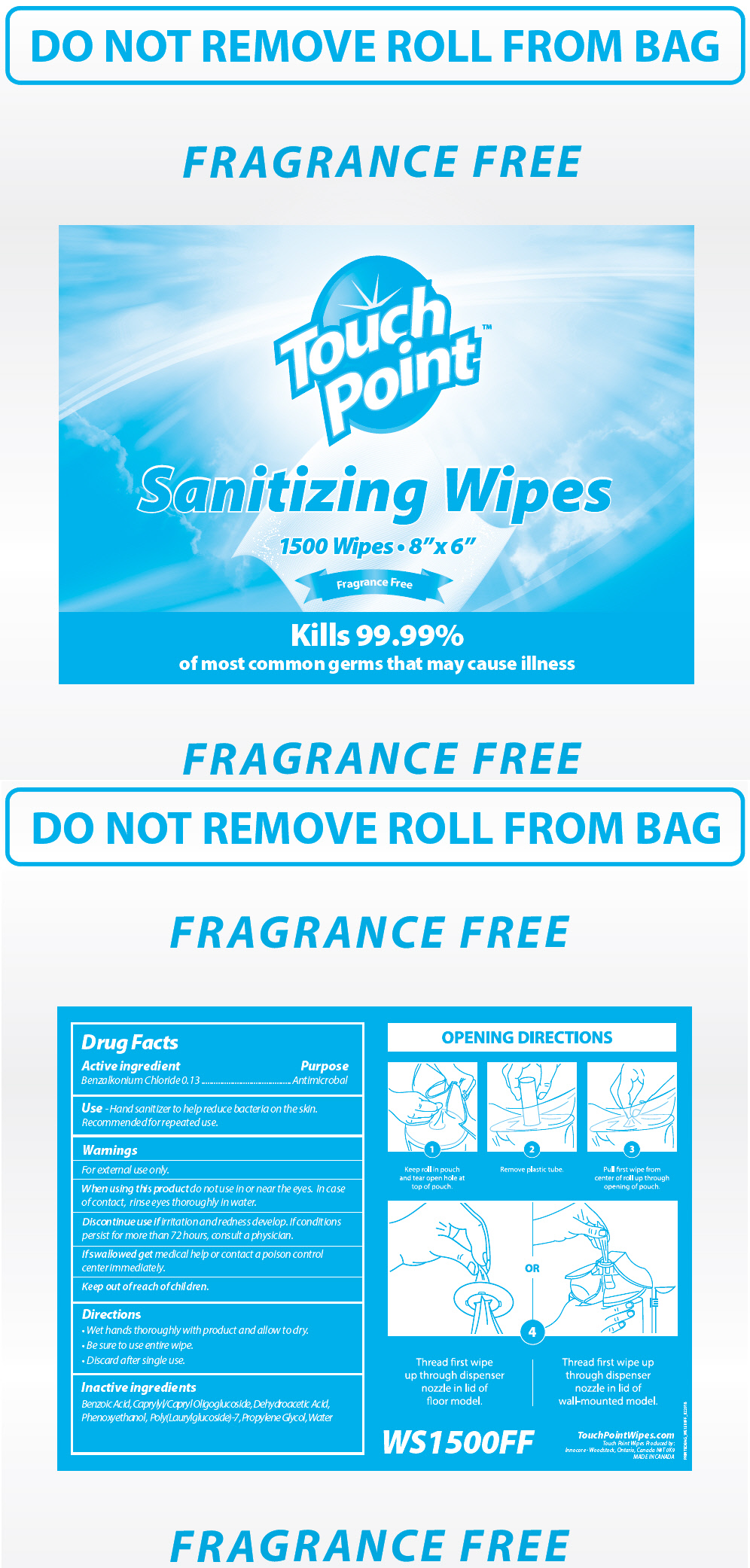 DRUG LABEL: Touchpoint Wipes Fragrance Free
NDC: 70924-002 | Form: CLOTH
Manufacturer: Innocore Sales & Marketing Inc
Category: otc | Type: HUMAN OTC DRUG LABEL
Date: 20250619

ACTIVE INGREDIENTS: BENZALKONIUM CHLORIDE 1.3 mg/1 1
INACTIVE INGREDIENTS: WATER; PROPYLENE GLYCOL; CAPRYLYL/CAPRYL OLIGOGLUCOSIDE; POLY(LAURYLGLUCOSIDE)-7; PHENOXYETHANOL; BENZOIC ACID; DEHYDROACETIC ACID

Touchpoint Wipes Fragrance Free
Sanitizing Wipes

Drug Facts

Active ingredient

Benzalkonium Chloride 0.13 %

Purpose

Antimicrobal

Use

Hand sanitizer to help reduce bacteria on the skin.

Recommended for repeated use.

Warnings

For external use only.

When using this product do not use in or near the eyes. In case of contact, rinse eyes thoroughly in water.

STOP USE

Discontinue use if irritation and redness develop. If conditions persist for more than 72 hours, consult a physician.

If swallowed get medical help or contact a poison control center immediately.

Keep out of reach of children.

Directions

- Wet hands thoroughly with product and allow to dry.
- Children under 6 years of age should be supervised when using this product.
- Be sure to use entire wipe.
- Discard after single use.

Inactive ingredients

Benzoic Acid, Caprylyl/Capryl Oligoglucoside, Dehydroacetic Acid, Phenoxyethanol, Poly(Laurylglucoside)-7, Propylene Glycol, Water

PACKAGE LABEL

Touch
Point™

Sanitizing Wipes

1500 Wipes • 8"x 6"

Fragrance Free

Kills 99.99%
of most common germs that may cause illness